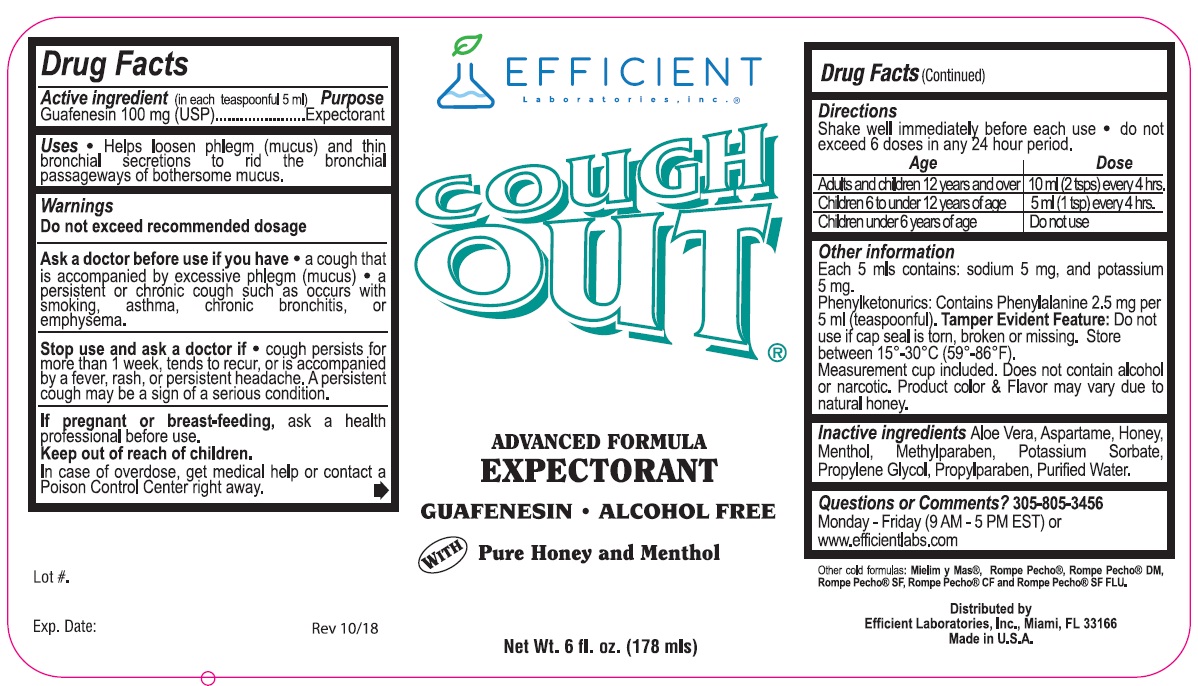 DRUG LABEL: Cough Out
NDC: 58593-255 | Form: LIQUID
Manufacturer: Efficient Laboratories Inc.
Category: otc | Type: HUMAN OTC DRUG LABEL
Date: 20250618

ACTIVE INGREDIENTS: GUAIFENESIN 100 mg/5 mL
INACTIVE INGREDIENTS: ALOE VERA LEAF; HONEY; MENTHOL; POTASSIUM SORBATE; PROPYLENE GLYCOL; PROPYLPARABEN; METHYLPARABEN; WATER; ASPARTAME

Cough Out

Active Ingredient: (In each teaspoonful 5 mls) Purpose

Guiafenesin 100 mg (USP)............................................Expectorant

Purpose Expectorant

Uses

Helps loosen phlegm (mucus) and thin bronchial secretions to rid the bronchial passageways of bothersome mucus.

Warnings

Do not exceed recommended dosage

Ask a doctor before use if you have

- a cough that is accompanied by excessive phlegm (mucus)
- a persistent or chronic cough such as occurs with smoking, asthma, chronic bronchitis, or emphysema.

Stop use and ask a doctor if

- cough persists for more than 1 week, tends to recur, or is accompanied by a fever, rash, or persstent headached. A persistent cough may be a sign of a serious condition.

Keep Out of Reach of Children.

In case of accidental overdose, get medical help or contact the Poison Control Center right away.

PREGNANCY OR BREAST FEEDING

If pregnant or breast-feeding,ask a health professional before use.

Directions:

Shake well immediately before use.

Do not exceed 6 doses in any 24 hour period.

Adults and Children 12 years and over - 10 ml (2 tsps) every 4 hours

Children 6 to under 12 years of age - 5 ml (1 tsp) every 4 hours

Children under 6 years of age - Do not use

INACTIVE INGREDIENT

Inactive Ingredients:Aloe Vera, Aspartame, Honey, Menthol, Methylparaben, Potassium Sorbate, Propylene Glycol, Propylparaben, Purified Water

OTHER SAFETY INFORMATION

Each 5 mls contains: sodium 5 mg, and potassium 5 mg

Phenylketonurics: Contains Phenylalanine 2.5 mg per 5 ml (teaspoonful).

Questions or Comments?

305.805.3456 Monday-Friday 9AM to 5PM EST

www.efficientlabs.com